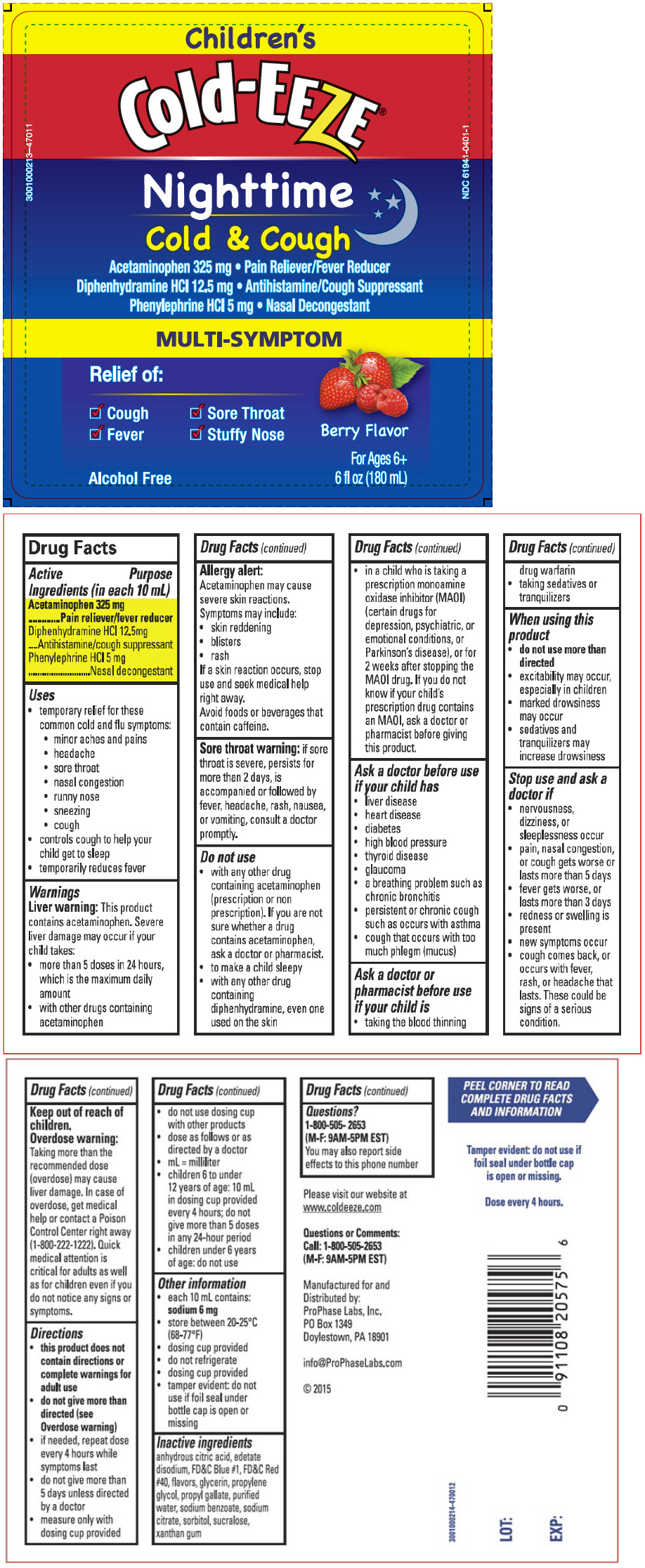 DRUG LABEL: Cold-EEZE 
NDC: 61941-0401 | Form: LIQUID
Manufacturer: ProPhase Labs, Inc.
Category: otc | Type: HUMAN OTC DRUG LABEL
Date: 20160129

ACTIVE INGREDIENTS: Acetaminophen 325 mg/10 mL; Diphenhydramine Hydrochloride 12.5 mg/10 mL; Phenylephrine Hydrochloride 5 mg/10 mL
INACTIVE INGREDIENTS: Anhydrous Citric Acid; Edetate Disodium; FD&C Blue NO. 1; FD&C Red NO. 40; Glycerin; Propylene Glycol; Propyl Gallate; Water; Sodium Benzoate; Sodium Citrate, Unspecified Form; Sorbitol; Sucralose; Xanthan Gum

Cold-EEZE®
Children's Nighttime Cold & Cough Relief

Drug Facts

ACTIVE INGREDIENT

Active Ingredients (in each 10 mL) | Purpose
Acetaminophen 325 mg | Pain reliever/fever reducer
Diphenhydramine HCl 12.5mg | Antihistamine/cough suppressant
Phenylephrine HCl 5 mg | Nasal decongestant

Uses

- temporary relief for these common cold and flu symptoms:
  - minor aches and pains
  - headache
  - sore throat
  - nasal congestion
  - runny nose
  - sneezing
  - cough
- controls cough to help your child get to sleep
- temporarily reduces fever

Warnings

Liver warning

This product contains acetaminophen. Severe liver damage may occur if your child takes:

- more than 5 doses in 24 hours, which is the maximum daily amount
- with other drugs containing acetaminophen

Allergy alert

Acetaminophen may cause severe skin reactions.
Symptoms may include:

- skin reddening
- blisters
- rash

If a skin reaction occurs, stop use and seek medical help right away.

Avoid foods or beverages that contain caffeine.

Sore throat warning: if sore throat is severe, persists for more than 2 days, is accompanied or followed by fever, headache, rash, nausea, or vomiting, consult a doctor promptly.

Do not use

- with any other drug containing acetaminophen (prescription or nonprescription). If you are not sure whether a drug contains acetaminophen, ask a doctor or pharmacist.
- to make a child sleepy
- with any other drug containing diphenhydramine, even one used on the skin
- in a child who is taking a prescription monoamine oxidase inhibitor (MAOI) (certain drugs for depression, psychiatric, or emotional conditions, or Parkinson's disease), or for 2 weeks after stopping the MAOI drug. If you do not know if your child's prescription drug contains an MAOI, ask a doctor or pharmacist before giving this product.

Ask a doctor before use if your child has

- liver disease
- heart disease
- diabetes
- high blood pressure
- thyroid disease
- glaucoma
- a breathing problem such as chronic bronchitis
- persistent or chronic cough such as occurs with asthma
- cough that occurs with too much phlegm (mucus)

Ask a doctor or pharmacist before use if your child is

- taking the blood thinning drug warfarin
- taking sedatives or tranquilizers

When using this product

- do not use more than directed
- excitability may occur, especially in children
- marked drowsiness may occur
- sedatives and tranquilizers may increase drowsiness

Stop use and ask a doctor if

- nervousness, dizziness, or sleeplessness occur
- pain, nasal congestion, or cough gets worse or lasts more than 5 days
- fever gets worse, or lasts more than 3 days
- redness or swelling is present
- new symptoms occur
- cough comes back, or occurs with fever, rash, or headache that lasts. These could be signs of a serious condition.

Keep out of reach of children.

Overdose warning

Taking more than the recommended dose (overdose) may cause liver damage. In case of overdose, get medical help or contact a Poison Control Center right away (1-800-222-1222). Quick medical attention is critical for adults as well as for children even if you do not notice any signs or symptoms.

Directions

- this product does not contain directions or complete warnings for adult use
- do not give more than directed (see Overdose warning)
- if needed, repeat dose every 4 hours while symptoms last
- do not give more than 5 days unless directed by a doctor
- measure only with dosing cup provided
- do not use dosing cup with other products
- dose as follows or as directed by a doctor
- mL = milliliter
- children 6 to under 12 years of age: 10 mL in dosing cup provided every 4 hours; do not give more than 5 doses in any 24-hour period
- children under 6 years of age: do not use

Other information

- each 10 mL contains: sodium 6 mg
- store between 20-25°C (68-77°F)
- dosing cup provided
- do not refrigerate
- dosing cup provided
- tamper evident: do not use if foil seal under bottle cap is open or missing

Inactive ingredients

anhydrous citric acid, edetate disodium, FD&C Blue #1, FD&C Red #40, flavors, glycerin, propylene glycol, propyl gallate, purified water, sodium benzoate, sodium citrate, sorbitol, sucralose, xanthan gum

Questions?

1-800-505-2653
(M-F: 9AM-5PM EST)
You may also report side effects to this phone number

Manufactured for and
Distributed by:
ProPhase Labs, Inc.
PO Box 1349
Doylestown, PA 18901

PRINCIPAL DISPLAY PANEL - 180 mL Bottle Label

Children's
Cold-EEZE®
Nighttime
Cold & Cough

3001000213--47011

NDC 61941-0401-1

Acetaminophen 325 mg • Pain Reliever/Fever Reducer

Diphenhydramine HCl 12.5 mg • Antihistamine/Cough Suppressant

Phenylephrine HCl 5 mg • Nasal Decongestant

MULTI-SYMPTOM

Relief of:

✓ Cough
✓ Sore Throat
✓ Fever
✓ Stuffy Nose

Alcohol Free

Berry Flavor

For Ages 6+
6 fl oz (180 mL)